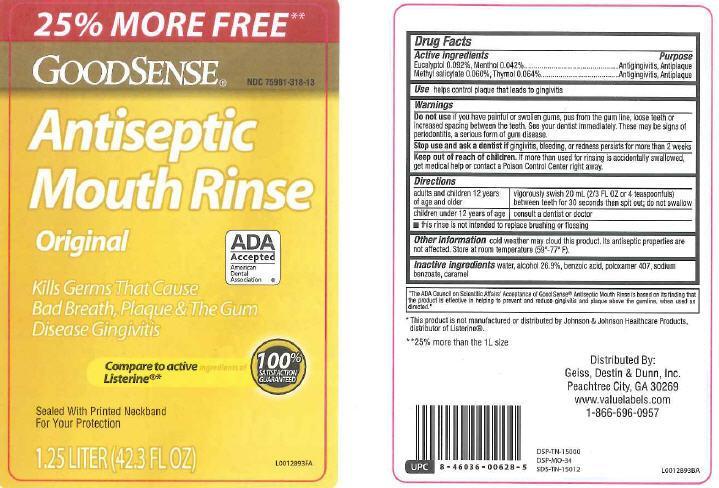 DRUG LABEL: Antiseptic
NDC: 75981-318 | Form: MOUTHWASH
Manufacturer: Geiss, Destin + Dunmn, Inc
Category: otc | Type: HUMAN OTC DRUG LABEL
Date: 20250221

ACTIVE INGREDIENTS: EUCALYPTOL 0.92 mg/1 mL; MENTHOL 0.42 mg/1 mL; METHYL SALICYLATE 0.6 mg/1 mL; THYMOL 0.64 mg/1 mL
INACTIVE INGREDIENTS: SODIUM BENZOATE; CARAMEL; WATER; ALCOHOL; BENZOIC ACID; POLOXAMER 407

Good Sense 318
Antiseptic Mouthrinse

Active ingredients

Eucalyptol 0.092%

Menthol 0.042%

Methyl saliclate 0.060%

Thymol 0.064%

Purpose

Antigingivitis, antiplaque

Use

Usehelps control plaque that leads to gingivitis

Warnings

Do not use

Do not useif you have painful or swollen gums, pus from the gun line, loose teeth or increased spacing between the teeth. See your dintist immediately. These may be sings of periodontitis, a serous form of gum disease.

Stop use

Stop use and ask a dentist ifgingivitis, bleeding or redness persists for more than 2 weeks

Keep out of reach of children. If more than used for rinsing is accidentally swallowed, get medical help or contact a Poison Control Center right away.

Directions

adults and children 12 years of age and older - vigorously swish 20 mL (2/3 FL OZ or 4 teaspoonsfuls) between teeth for 30 seconds then spit out; do not swallow

Children under 12 years of age - consult a dentist or doctor

- this rinse is not intended to replace brushing or flossing

Other information

Other information cold weather may cloud this product. Its antiseptic properites are not affected. Store at room temperature (59°-77°F).

Inactive ingredients

Inactive ingredientswater, alcohol 26.9%, benzoic acid, poloxamer 407, sodium benzoate, caramel

ADA Information

The ADA Council on Scientific Affairs of Good Sense Antiseptic Mouth Rinse is based on the finding that the product is effective in helping to prevent and reduce gingivitis and plaque above the gumline, when used as directed

Disclaimer

This product is not manufactured or distributed by Johnson + Johnson Healthcare Products, distributor of Listerine.

25% more than the 1 L size

Adverse reaction section

Distributed by:

Geiss, Destin + Dunn, Inc

Peachtree City, GA 30269

www.valuelabels.com

1-866-696-0957

DSP-TN-15000

DSP-MO-34

SDA-TN 15012

Principal display panel

25% MORE FREE

GoodSense

Antiseptic

Mouth Rinse

Original

ADA

Accepted

American Dental Association

Kills Germs That Cause

Bad Breath, Plaque + The Gum Disease Gingivitis

Compare to active ingredient of Listerine

Sealed With Printed Neckband For Your Protection

1.25 Liter (42.3 FL OZ)